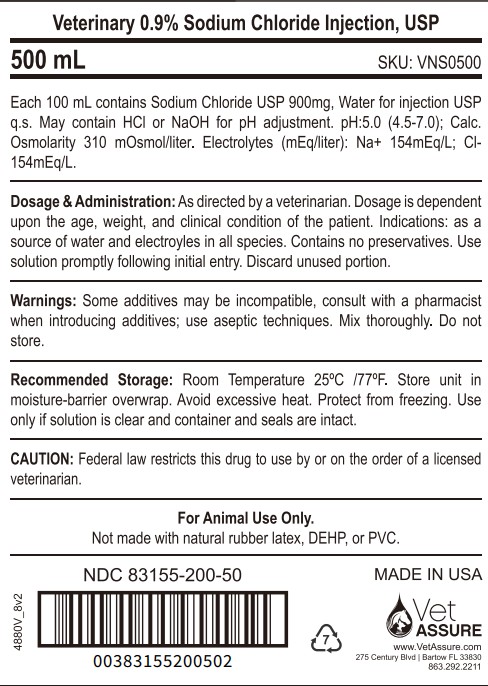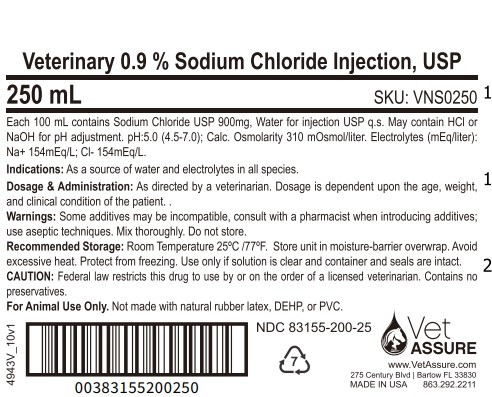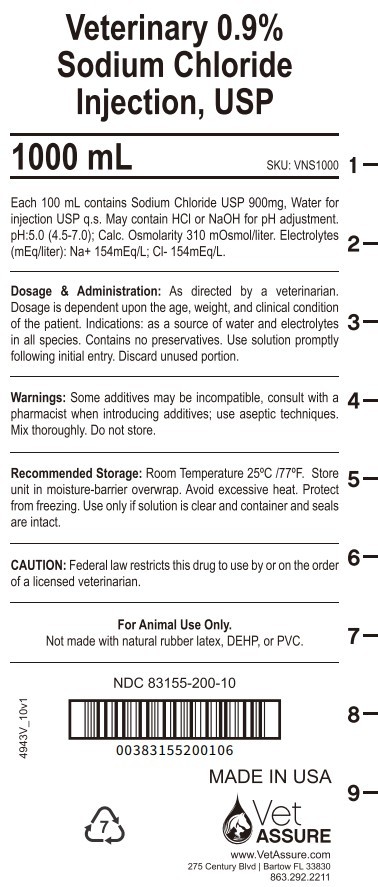 DRUG LABEL: Veterinary 0.9% Sodium Chloride
NDC: 83155-200 | Form: INJECTION, SOLUTION
Manufacturer: Assure Infusions, Inc
Category: animal | Type: PRESCRIPTION ANIMAL DRUG LABEL
Date: 20250609

ACTIVE INGREDIENTS: SODIUM CHLORIDE 900 mg/100 mL
INACTIVE INGREDIENTS: WATER

Veterinary Sodium Chloride Injection, USP

For Animal Use Only

Description

Veterinary 0.9% Sodium Chloride Injection, USP is a sterile, nonpyrogenic solution for fluid and electrolyte replenishment in single dose containers for parenteral administration. It contains no antimicrobial agents. Discard unused portion.

Clinical Pharmacology

Veterinary 0.9% Sodium Chloride Injection, USP has value as a source of water and electrolytes. It is capable of inducing diuresis depending on the clinical condition

of the patient.

Indications and Usage

Veterinary 0.9% Sodium Chloride Injection, USP is indicated as a source of water and electrolytes.

Contraindications

None known.

Warnings

Sodium Chloride Injection, USP should be used with great care, if at all, in patients with congestive heart failure, severe renal insufficiency, and in clinical states in which there exists edema with sodium retention.

The intravenous administration of Sodium Chloride Injection, USP can cause fluid and/or solute overloading resulting in dilution of serum electrolyte concentrations, overhydration, congested states, or pulmonary edema. The risk of dilutive states is inversely proportional to the electrolyte concentration of the injections. The risk of solute overload causing congested states with peripheral and pulmonary edema is directly proportional to the electrolyte concentrations of the injections.

In patients with diminished renal function, administration of Sodium Chloride Injection, USP may result in sodium retention.

Adverse Reactions

Reactions which may occur because of the solution or the technique of administration include febrile response, infection at the site of injection, venous thrombosis or phlebitis extending from the site of injection, extravasation, and hypervolemia. If an adverse reaction does occur, discontinue the infusion, evaluate the patient, institute appropriate therapeutic countermeasures, and save the remainder of the fluid for examination if deemed necessary.

Precautions

Clinical evaluation and periodic laboratory determinations are necessary to monitor changes in fluid balance, electrolyte concentrations, and acid base balance during prolonged parenteral therapy or whenever the condition of the patient warrants such evaluation.
Caution must be exercised in the administration of Veterinary 0.9% Sodium Chloride Injection, USP to patients receiving corticosteroids or corticotropin. Do not administer unless solution is clear and seal is intact.

Dosage and Administration

As directed by a veterinarian. Dosage is dependent upon the age, weight and clinical condition of the patient, as well as laboratory determinations.
Parenteral drug products should be inspected visually for particulate matter and discoloration prior to administration whenever solution and container permit.
All solutions for injection contained in plastic containers are intended for administration using sterile equipment and aseptic technique. Additives may be incompatible. Complete information is not available. Those additives known to be incompatible should not be used. Consult with pharmacist, if available. If, in the informed judgment of the veterinarian, it is deemed advisable to introduce additives, use aseptic technique. Mix thoroughly when additives have been introduced.
Do not store solutions containing additives. Discard unused portion.

Over Dosage

In an event of overhydration or solute overload, re-evaluate the patient and institute appropriate corrective measures.
See Warnings, Adverse Reactions and Precautions.

How Supplied

Veterinary 0.9% Sodium Chloride Injection, USP is supplied in plastic bags as follows:
The plastic container is fabricated from a multi-layer, Polyolefin/Styrene-block copolymer film. The amount of water that can permeate from inside the container into the overwrap is insufficient to affect the solution significantly.

Storage:

Exposure of pharmaceutical products to heat should be minimized. Avoid excessive heat. It is recommended the product be stored in the moisture overwrap at room temperature (25ºC/77ºF); brief exposure up to (40ºC/104ºF) does not adversely affect the product.

Directions for use of plastic container

To Open
Tear overwrap down side at slit and remove solution bag. Some opacity of the plastic due to moisture absorption during the sterilization process may be observed.
This is normal and does not affect the solution quality or safety.The opacity will diminish gradually. Check for minute leaks by squeezing inner bag firmly. If leaks
are found, discard solution as sterility may be impaired. If supplemental medication is desired, follow directions below.
Preparation for Administration
1. Suspend container from eyelet support.
2. Remove protector from outlet port at bottom of container.
3. Attach administration set. Refer to complete directions accompanying set.
To Add Medication
WARNING: Additives may be incompatible.
To add medication before solution administration
1. Prepare medication site.
2. Using syringe with 19 to 22 gauge needle, puncture resealable medication port and inject.
3. Mix solution and medication thoroughly. For high density medication such as potassium chloride, turn bag so ports are upright, and no liquid remains in
ports and mix thoroughly.
To add medication during solution administration
1. Close clamp on the administration set to stop the flow to the patient.
2. Prepare medication port.
3. Using syringe with 19 to 22 gauge needle, puncture resealable medication port and inject.
4. Remove container from IV pole and/or turn to an upright position.
5. Evacuate both ports while container is in the upright position.
6. Mix solution and medication thoroughly.
7. Return container to in-use position and continue administration.